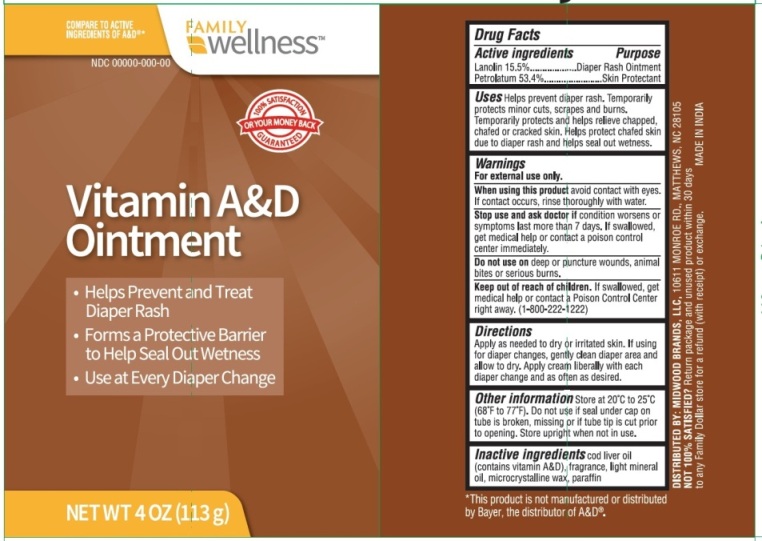 DRUG LABEL: Vitamin A and D
NDC: 55319-103 | Form: OINTMENT
Manufacturer: Family Dollar Services Inc
Category: otc | Type: HUMAN OTC DRUG LABEL
Date: 20171108

ACTIVE INGREDIENTS: LANOLIN 15.5 g/100 g; PETROLATUM 53.4 g/100 g
INACTIVE INGREDIENTS: COD LIVER OIL; LIGHT MINERAL OIL; MICROCRYSTALLINE WAX; PARAFFIN

Vitamin A and D Ointment

Active Ingredients

Lanolin 15.5%

Petrolatum 53.4%

Purpose

Diaper Rash Ointment

Skin Protectant

Uses

Helps prevent diaper rash. Temporarily protects minor cuts, scrapes and burns. Temporarily protects and helps relieve chapped, chafed or cracked skin. Helps protect chafed skin due to diaper rash and helps seal out wetness.

Warnings

For external use only.

When using this product avoid contact with eyes. If contact occurs, rinse thoroughly with water.

Stop use and ask doctor if condition worsens or symptoms last more than 7 days. If swallowed, get medical help or contact a poison control center immediately.

Do not use on deep or puncture wounds, animal bites or serious burns.

Keep out of reach of children. If swallowed, get medical help or contact a Poison Control Center right away (1-800-222-1222).

DOSAGE AND ADMINISTRATION

Direction

Apply as needed to dry or irritated skin. If using for diaper changes, gently clean diaper area and allow to dry. Apply cream liberally with each diaper change and as often as desired.

Other Information

Store at 20°C to 25°C (68°F to 77°F). Do not use if seal under cap on tube is broken, missing or if tube tip is cut prior to opening. Store upright when not in use.

Inactive Ingredients

Cod liver oil (contains vitamin A&D), fragrance, light mineral oil, microcrystalline wax, paraffin

PACKAGE LABEL

PRINCIPAL DISPLAY PANEL